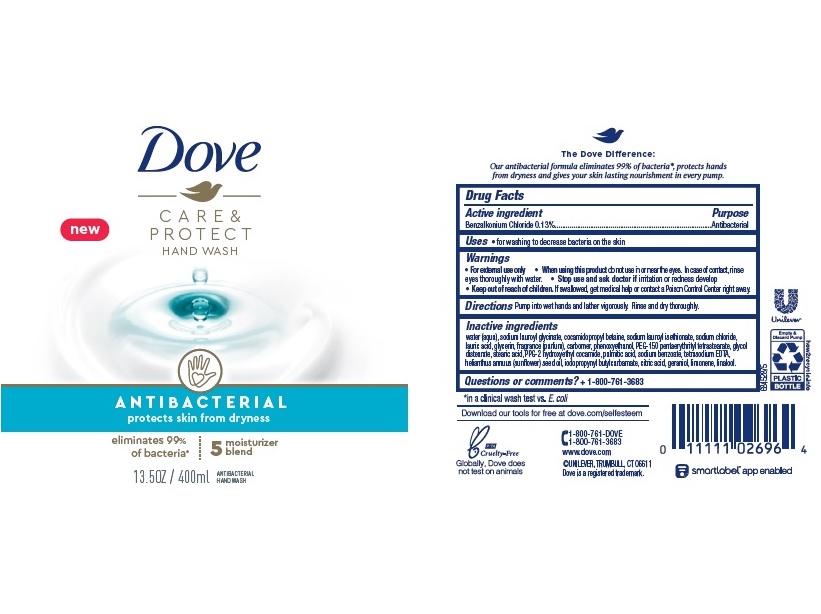 DRUG LABEL: Dove
NDC: 64942-1847 | Form: LIQUID
Manufacturer: Conopco Inc. d/b/a/ Unilever
Category: otc | Type: HUMAN OTC DRUG LABEL
Date: 20240816

ACTIVE INGREDIENTS: BENZALKONIUM CHLORIDE 1.3 mg/1 mL
INACTIVE INGREDIENTS: PEG-150 PENTAERYTHRITYL TETRASTEARATE; SODIUM LAUROYL GLYCINATE; STEARIC ACID; SODIUM CHLORIDE; CITRIC ACID MONOHYDRATE; WATER; GLYCERIN; COCAMIDOPROPYL BETAINE; PALMITIC ACID; EDETATE SODIUM; SODIUM BENZOATE; SODIUM LAUROYL ISETHIONATE; CARBOMER HOMOPOLYMER, UNSPECIFIED TYPE; PHENOXYETHANOL; PPG-2 HYDROXYETHYL COCAMIDE; LAURIC ACID; IODOPROPYNYL BUTYLCARBAMATE; SUNFLOWER OIL; GLYCOL DISTEARATE

Dove Care & Protect Antibacterial Hand Wash

DOVE CARE & PROTECT ANTIBACTERIAL HAND WASH - Benzalkonium Chloride

Dove Care & Protect Antibacterial Hand Wash

Drug Facts

Active ingredient

Benzalkonium Chloride 0.13%

Purpose

Antibacterial

Uses

For washing to decrease bacteria on the skin

Warnings

• For external use only
• When using this product do not use in or near the eyes. In case of contact, rinse eyes thoroughly with wate r
• Stop use and ask doctor if irritation or redness develop.

• Keep out of reach of children except under adult supervision.

If swallowed, get medical help or contact a poison control Center right away.

Directions

Pump into wet hands and lather vigorously. Rinse and dry thoroughly.

Inactive ingredients

Water (Aqua), Sodium Lauroyl Glycinate, Cocamidopropyl Betaine, Sodium Lauroyl Isethionate, Sodium Chloride, Lauric Acid, Glycerin, Fragrance (Parfum), Carbomer, Phenoxyethanol, PEG-150 Pentaerythrityl Tetrastearate, Glycol Distearate, Stearic Acid, PPG-2 Hydroxyethyl Cocamide, Palmitic Acid, Sodium Benzoate, Tetrasodium EDTA, Helianthus Annuus (Sunflower) Seed Oil, Iodopropynyl Butylcarbamate, Citric Acid, Geraniol, Limonene, Linalool.

Questions or Comments?

1-800-761-3683